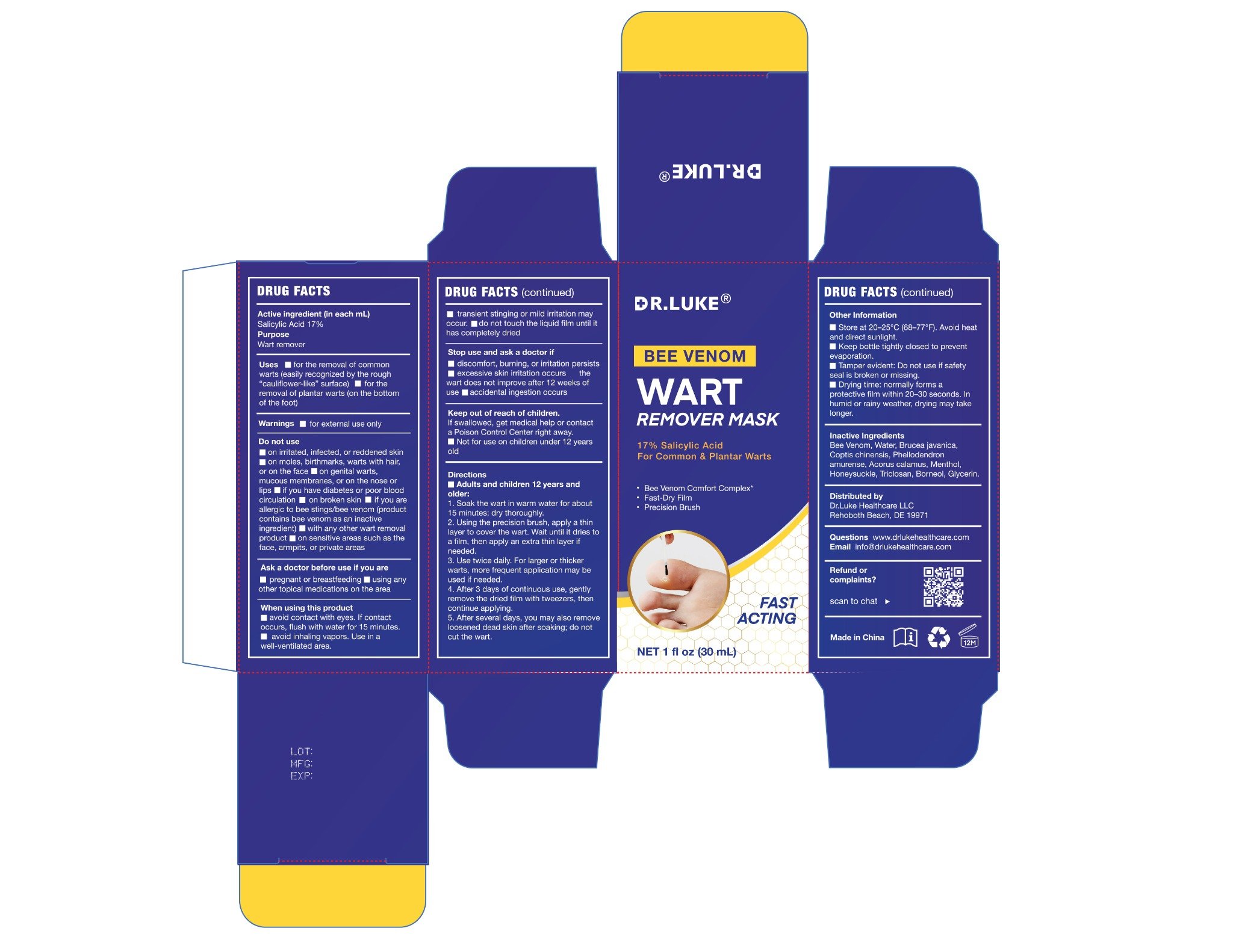 DRUG LABEL: Dr. Luke Bee Venom Wart and Corn Remover
NDC: 87147-010 | Form: SOLUTION
Manufacturer: DANOUS LAND FLOOW LLC
Category: otc | Type: HUMAN OTC DRUG LABEL
Date: 20251210

ACTIVE INGREDIENTS: SALICYLIC ACID 170 mg/1000 mL
INACTIVE INGREDIENTS: COPTIS CHINENSIS ROOT; PHELLODENDRON AMURENSE BARK; MENTHOL; GLYCERIN; WATER; BORNEOL; BRUCEA JAVANICA FRUIT; ACORUS CALAMUS ROOT; TRICLOSAN; APIS MELLIFERA VENOM; LONICERA JAPONICA FLOWER

Drug Facts

Active ingredient

Salicylic Acid 17%

Purpose

Wart remover

Uses

- for the removal of common warts (easily recognized by the rough “cauliflower-like” surface)
- for the removal of plantar warts (on the bottom of the foot)

Warnings

for external use only

Do not use

- on irritated, infected, or reddened skin
- on moles, birthmarks, warts with hair, or on the face
- on genital warts, mucous membranes, or on the nose or lips
- if you have diabetes or poor blood circulation
- on broken skin
- if you are allergic to bee stings/bee venom (product contains bee venom as an inactive ingredient)
- with any other wart removal product
- on sensitive areas such as the face, armpits, or private areas

Ask a doctor before use if you are

- pregnant or breastfeeding
- using any other topical medications on the area

When using this product

- avoid contact with eyes. If contact occurs, flush with water for 15 minutes.
- avoid inhaling vapors. Use in a well-ventilated area.
- transient stinging or mild irritation may occur.
- do not touch the liquid film until it has completely dried.

Stop use and ask a doctor if

- discomfort, burning, or irritation persists
- excessive skin irritation occurs
- the wart does not improve after 12 weeks of use
- accidental ingestion occurs

Keep out of reach of children.

- If swallowed, get medical help or contact a Poison Control Center right away.
- Not for use on children under 12 years old.

Directions

1. Soak the wart in warm water for about 15 minutes; dry thoroughly.
2. Using the precision brush, apply a thin layer to cover the wart. Wait until it dries to a film, then apply an extra thin layer if needed.
3. Use twice daily. For larger or thicker warts, more frequent application may be used if needed.
4. After 3 days of continuous use, gently remove the dried film with tweezers, then continue applying.
5. After several days, you may also remove loosened dead skin after soaking; do not cut the wart.

Other Information

- Store at 20–25°C (68–77°F). Avoid heat and direct sunlight.
- Keep bottle tightly closed to prevent evaporation.
- Tamper evident: Do not use if safety seal is broken or missing.
- Drying time: normally forms a protective film within 20–30 seconds. In humid or rainy weather, drying may take longer.

Inactive Ingredients

Bee Venom, Water, Brucea javanica, Coptis chinensis, Phellodendron amurense, Acorus calamus, Menthol, Honeysuckle, Triclosan, Borneol, Glycerin.

Questions

www.drlukehealthcare.com
Email info@drlukehealthcare.com